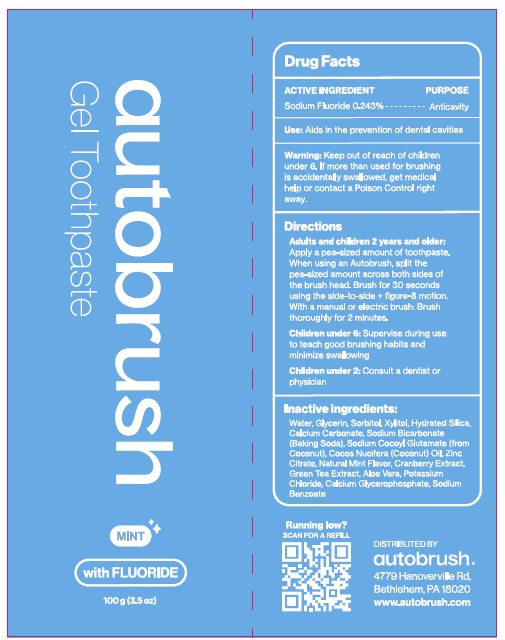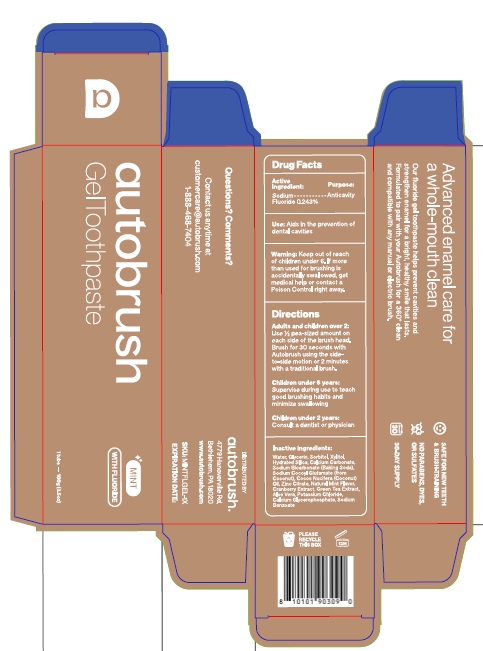 DRUG LABEL: AutoBrush Mint
NDC: 82913-006 | Form: GEL
Manufacturer: Lander Enterprises, LLC
Category: otc | Type: HUMAN OTC DRUG LABEL
Date: 20260203

ACTIVE INGREDIENTS: SODIUM FLUORIDE 0.243 g/100 g
INACTIVE INGREDIENTS: WATER; GLYCERIN; SORBITOL; XYLITOL; HYDRATED SILICA; CALCIUM CARBONATE; SODIUM BICARBONATE; SODIUM COCOYL GLUTAMATE; CALCIUM GLYCEROPHOSPHATE; COCOS NUCIFERA (COCONUT) OIL; POTASSIUM CHLORIDE; SODIUM BENZOATE; ZINC CITRATE; CRANBERRY JUICE; GREEN TEA LEAF; ALOE VERA LEAF

Active Ingredient

Sodium Fluoride 0.243%

Purpose

Anticavity

Uses

Aids in the prevention of dental cavities.

Warnings

Keep out of reach of children under 6 years of age. If more than used for brushing
is accidentally swallowed, get medical help or contact a Poison Control Central right away.

Directions

Adults and children 2 years and older:
Apply a pea-sized amount of toothpaste. When using an autobrush, split the pea-sized amount evenly across both sides of the brush head. Brush for 30 seconds using a side-to-side or figure-8 motion. With a manual or electric toothbrush, brush thoroughly for 2 minutes.

Children under 6:
Supervise brushing to teach good brushing habits and minimize swallowing.

Children under 2:
Consult a dentist or physician.

Inactive Ingredients

Water, Glycerin, Sorbitol, Xylitol, Hydrated Silica, Calcium Carbonate, Sodium Bicarbonate (Baking Soda), Sodium Cocoyl Glutamate (from Coconut), Cocos Nucifera (Coconut) Oil, Zinc Citrate, Natural Mint Flavor, Cranberry Extract, Green Tea Extract, Aloe Vera, Potassium Chloride, Calcium Glycerophosphate, Sodium Benzoate.